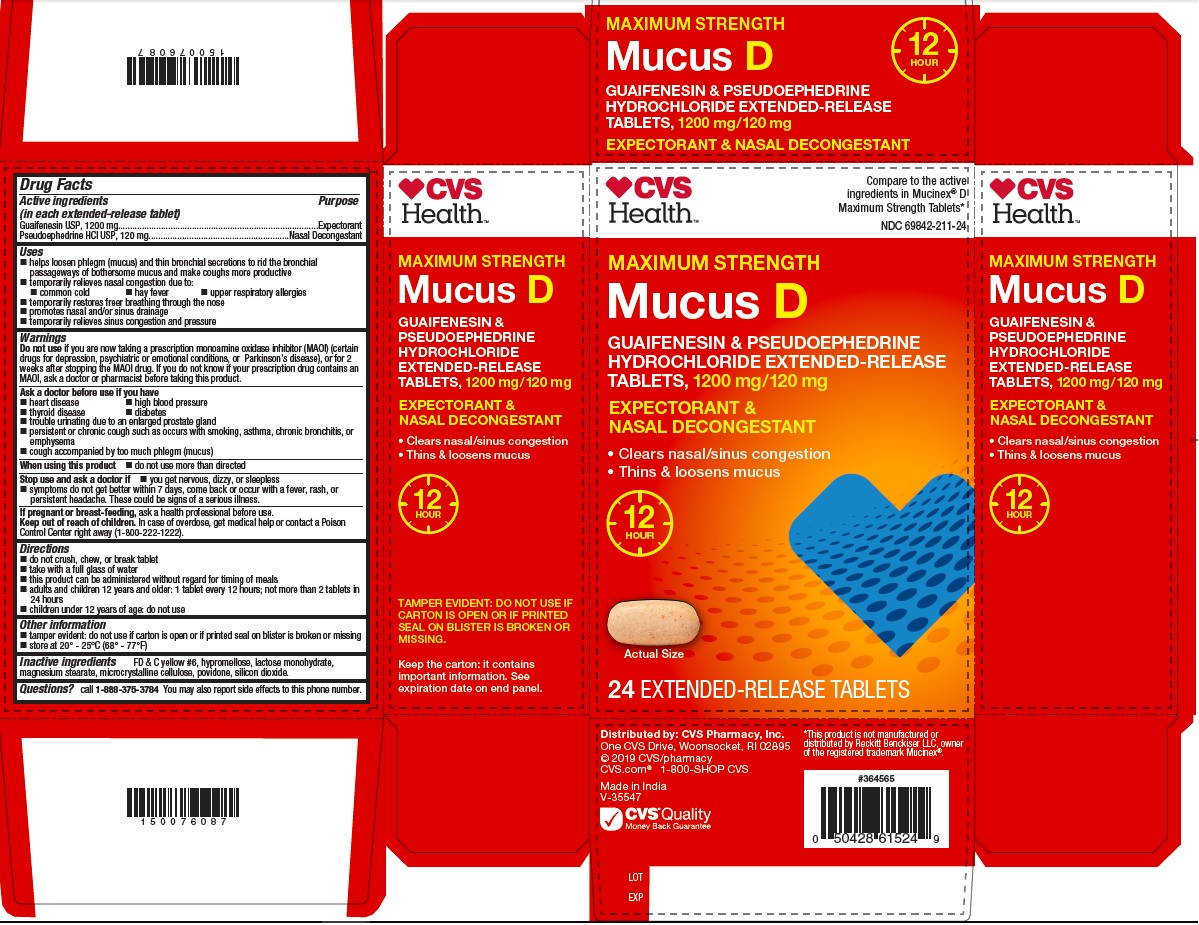 DRUG LABEL: Mucus Relief D
NDC: 69842-211 | Form: TABLET, EXTENDED RELEASE
Manufacturer: CVS Health Corp
Category: otc | Type: HUMAN OTC DRUG LABEL
Date: 20251210

ACTIVE INGREDIENTS: Guaifenesin 1200 mg/1 1; Pseudoephedrine Hydrochloride 120 mg/1 1
INACTIVE INGREDIENTS: FD&C YELLOW NO. 6; HYPROMELLOSES; LACTOSE MONOHYDRATE; MAGNESIUM STEARATE; CELLULOSE, MICROCRYSTALLINE; POVIDONE; SILICON DIOXIDE

Drug Facts

Active ingredients (in each extended-release tablet)

Guaifenesin USP, 1200 mg................................................................................Expectorant

Pseudoephedrine HCl USP, 120 mg......................................................Nasal Decongestant

Purpose

Expectorant and Nasal Decongestant

Uses

- helps loosen phlegm (mucus) and thin bronchial secretions to rid the bronchial passageways of bothersome mucus and make coughs more productive
- temporarily relieves nasal congestion due to:
  - common cold
  - hay fever
  - upper respiratory allergies
- temporarily restores freer breathing through the nose
- promotes nasal and/or sinus drainage
- temporarily relieves sinus congestion and pressure

Warnings

Do not use

if you are now taking a prescription monoamine oxidase inhibitor (MAOI) (certain drugs for depression, psychiatric, or emotional conditions, or Parkinson’s disease), or for 2 weeks after stopping the MAOI drug. If you do not know if your prescription drug contains an MAOI, ask a doctor or pharmacist before taking this product.

Ask a doctor before use if you have

- heart disease
- high blood pressure
- thyroid disease
- diabetes
- trouble urinating due to an enlarged prostate gland
- persistent or chronic cough such as occurs with smoking, asthma, chronic bronchitis, or emphysema
- cough accompanied by too much phlegm (mucus)

When using this product

- do not use more than directed

Stop use and ask doctor if

- you get nervous, dizzy, or sleepless
- symptoms do not get better within 7 days, come back or occur with a fever, rash, or persistent headache. These could be signs of a serious illness.

If pregnant or breast-feeding,

ask a health professional before use.

Keep out of reach of children.

In case of overdose, get medical help or contact a Poison Control Center right away (1-800-222-1222).

Directions

- do not crush, chew, or break tablet
- take with a full glass of water
- this product can be administered without regard for timing of meals
- adults and children 12 years and older: 1 tablet every 12 hours; not more than 2 tablets in 24 hours
- children under 12 years of age: do not use

Other information

- tamper evident: do not use if carton is open or if printed seal on blister is broken or missing
- store between 20° - 25°C (68° - 77°F)

Inactive ingredients

FD & C yellow #6, hypromellose, lactose monohydrate, magnesium stearate, microcrystalline cellulose, povidone, silicon dioxide.

Questions?

call 1-888-375-3784

You may also report side effect to this phone number.

Principal Display Panel

Guaifenesin and Pseudoephedrine HCl ER Tablets 1200 mg/120 mg: